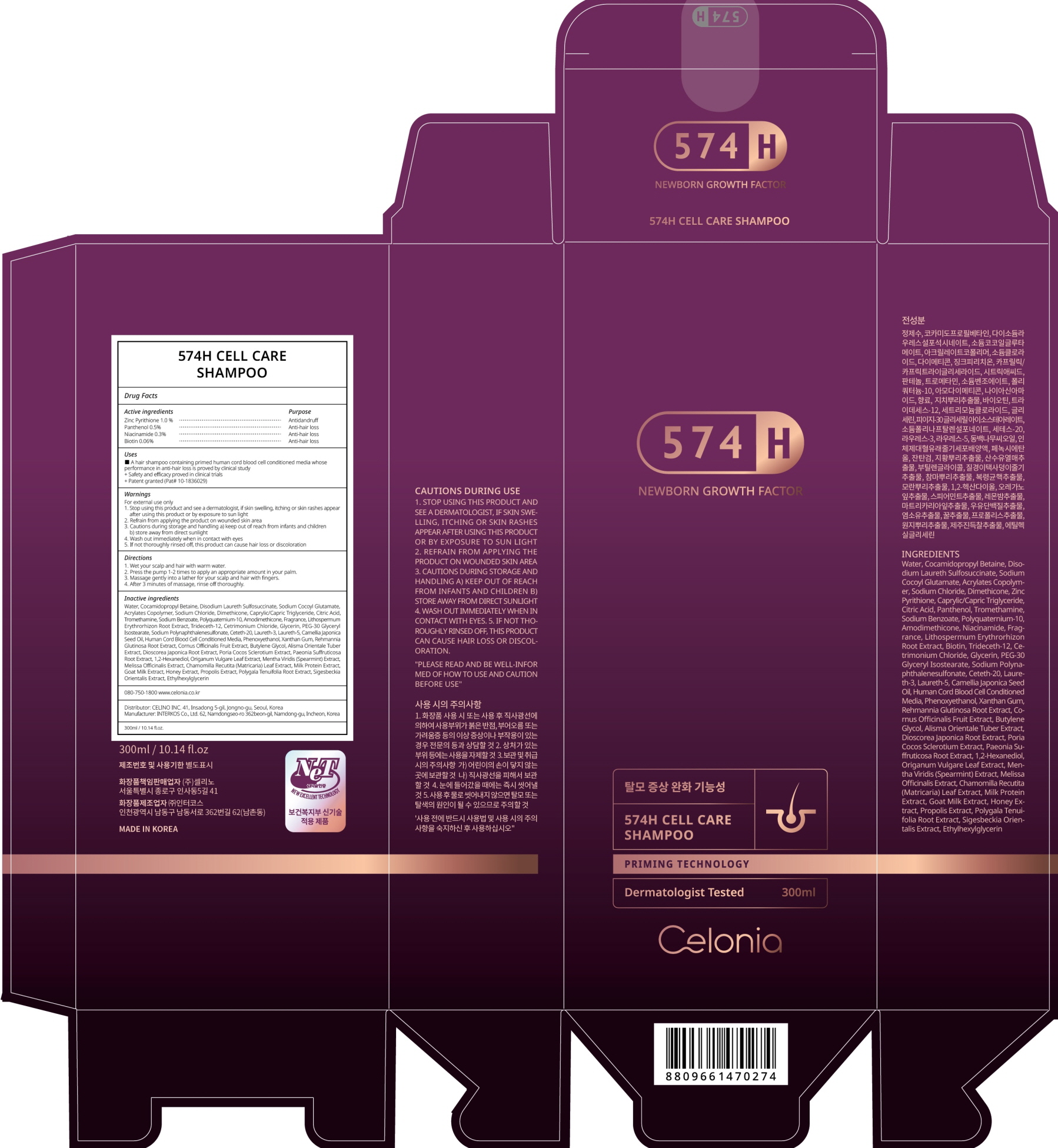 DRUG LABEL: 574H Cell Care
NDC: 73655-100 | Form: SHAMPOO
Manufacturer: Celino Inc.
Category: otc | Type: HUMAN OTC DRUG LABEL
Date: 20200619

ACTIVE INGREDIENTS: PYRITHIONE ZINC 3.0 g/300 mL; Panthenol 1.5 g/300 mL; Niacinamide 0.9 g/300 mL; Biotin 0.18 g/300 mL
INACTIVE INGREDIENTS: Water; Cocamidopropyl Betaine; Disodium Laureth Sulfosuccinate

ACTIVE INGREDIENTS

Zinc Pyrithione 1.0 %
Panthenol 0.5%
Niacinamide 0.3%
Biotin 0.06%

INACTIVE INGREDIENTS

Water, Cocamidopropyl Betaine, Disodium Laureth Sulfosuccinate, Sodium Cocoyl Glutamate, Acrylates Copolymer, Sodium Chloride, Dimethicone, Caprylic/Capric Triglyceride, Citric Acid, Tromethamine, Sodium Benzoate, Polyquaternium-10, Amodimethicone, Fragrance, Lithospermum Erythrorhizon Root Extract, Trideceth-12, Cetrimonium Chloride, Glycerin, PEG-30 Glyceryl Isostearate, Sodium Polynaphthalenesulfonate, Ceteth-20, Laureth-3, Laureth-5, Camellia Japonica Seed Oil, Human Cord Blood Cell Conditioned Media, Phenoxyethanol, Xanthan Gum, Rehmannia Glutinosa Root Extract, Cornus Officinalis Fruit Extract, Butylene Glycol, Alisma Orientale Tuber Extract, Dioscorea Japonica Root Extract, Poria Cocos Sclerotium Extract, Paeonia Suffruticosa Root Extract, 1,2-Hexanediol, Origanum Vulgare Leaf Extract, Mentha Viridis (Spearmint) Extract, Melissa Officinalis Extract, Chamomilla Recutita (Matricaria) Leaf Extract, Milk Protein Extract, Goat Milk Extract, Honey Extract, Propolis Extract, Polygala Tenuifolia Root Extract, Sigesbeckia Orientalis Extract, Ethylhexylglycerin

PURPOSE

Antidandruff, Anti-hair loss

WARNINGS

For external use only
1. Stop using this product and see a dermatologist, if skin swelling, itching or skin rashes appear after using this product or by exposure to sun light
2. Refrain from applying the product on wounded skin area
3. Cautions during storage and handling a) keep out of reach from infants and children b) store away from direct sunlight
4. Wash out immediately when in contact with eyes
5. If not thoroughly rinsed off, this product can cause hair loss or discoloration

KEEP OUT OF REACH OF CHILDREN

keep out of reach from infants and children

Uses

A hair shampoo containing primed human cord blood cell conditioned media whose performance in anti-hair loss is proved by clinical study
+ Safety and efficacy proved in clinical trials
+ Patent granted (Pat# 10-1836029)

Directions

1. Wet your scalp and hair with warm water.
2. Press the pump 1-2 times to apply an appropriate amount in your palm.
3. Massage gently into a lather for your scalp and hair with fingers.
4. After 3 minutes of massage, rinse off thoroughly.

QUESTIONS

080-750-1800 www.celonia.co.kr